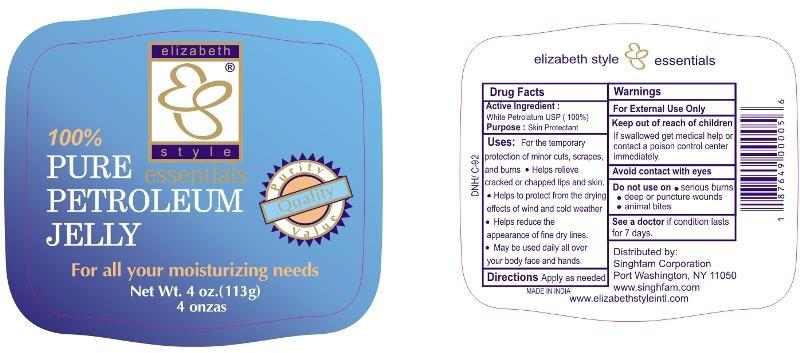 DRUG LABEL: Pure Petroleum
NDC: 52920-121 | Form: JELLY
Manufacturer: Singhfam Corporation
Category: otc | Type: HUMAN OTC DRUG LABEL
Date: 20121003

ACTIVE INGREDIENTS: PETROLATUM 1 g/1 g

Active ingredient

White Petrolatum USP (100 %)

Purpose

Skin Protectant

Uses

For the temporary protection of minor cuts, scrapes and burns.

- Helps relieve cracked or chapped lips and skin.
- Helps to protect from the drying effects of wind and cold weather.
- Helps reduce the appearance of fine dry lines.
- May be used daily all over your body, face and hands.

Warnings

For External Use Only.

Keep out of reach of children.

If swallowed get medical help or contact a poison control center immediately.

When using this product

Avoid contact with eyes.

Do not use on

- serious burns
- deep or puncture wounds
- animal bites

STOP USE

See a doctor if condition lasts for 7 days.

Directions

Apply as needed.

Inactive ingredients

None

PACKAGE LABEL

PRINCIPAL DISPLAY PANEL

100% PURE PETROLEUM JELLY
For all your moisturizing needs
Net Wt. 4 oz. (113g) 4 onzas